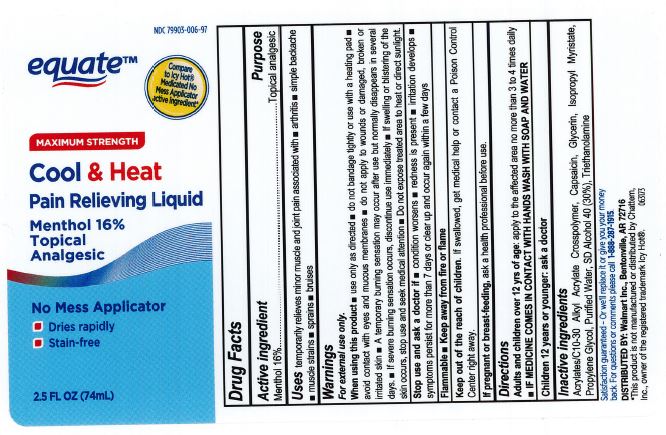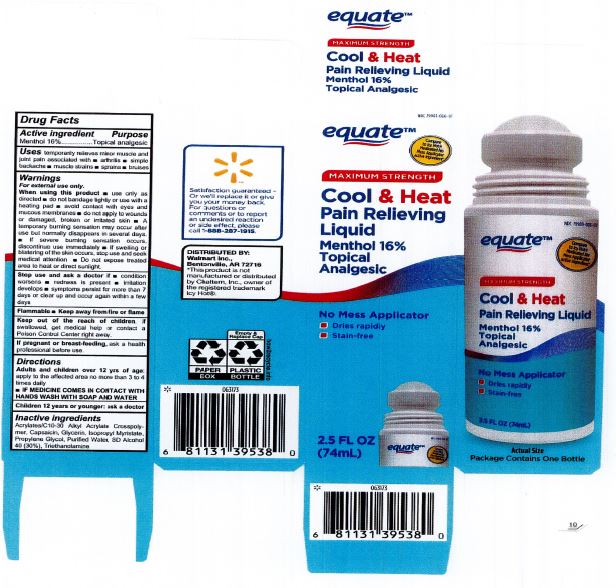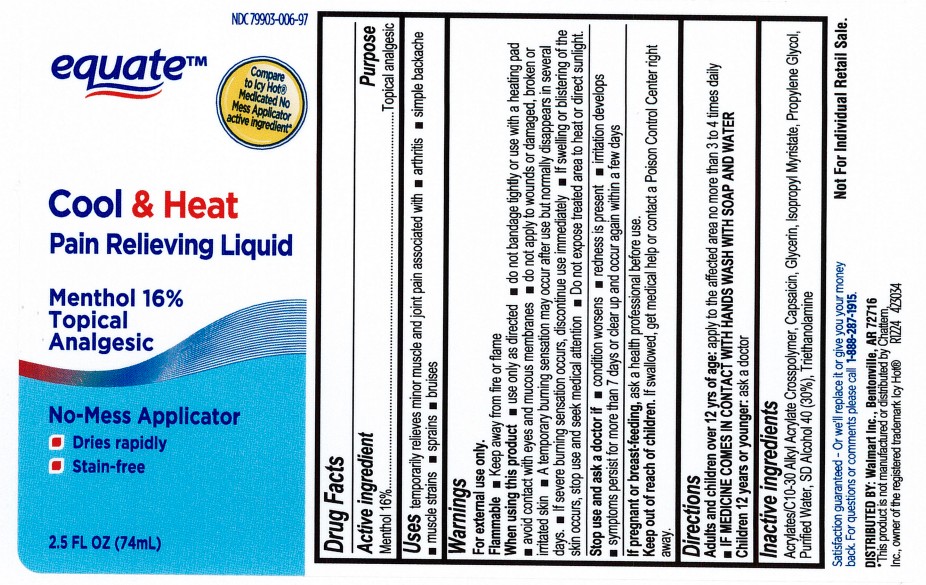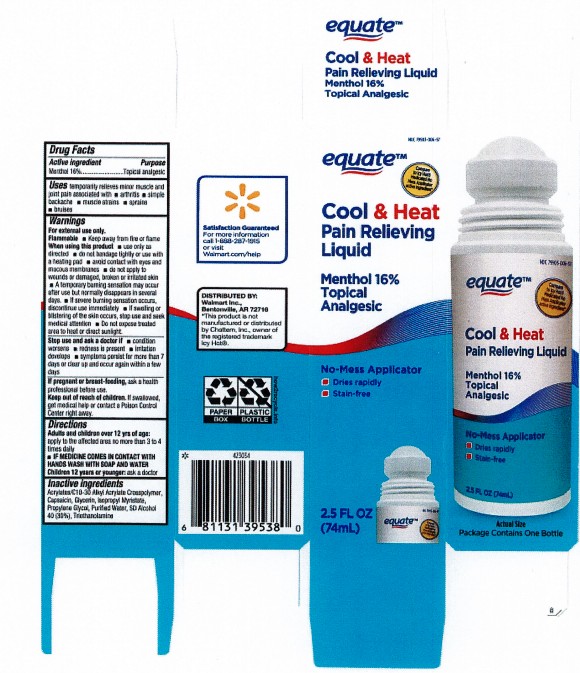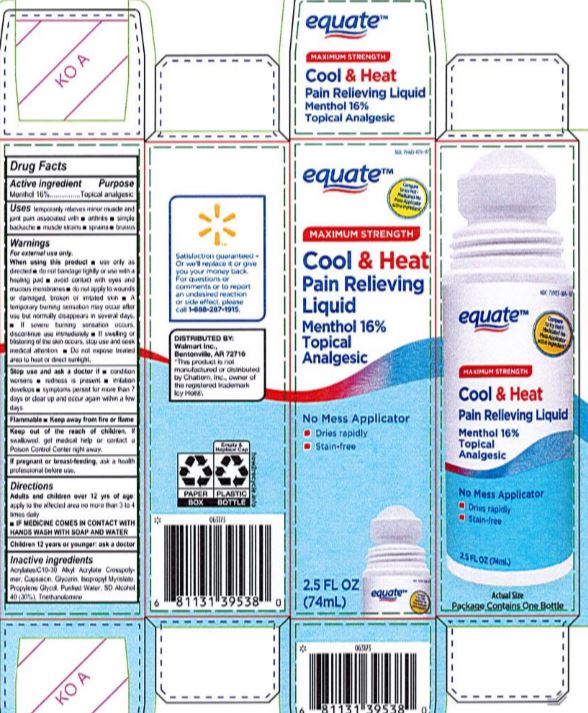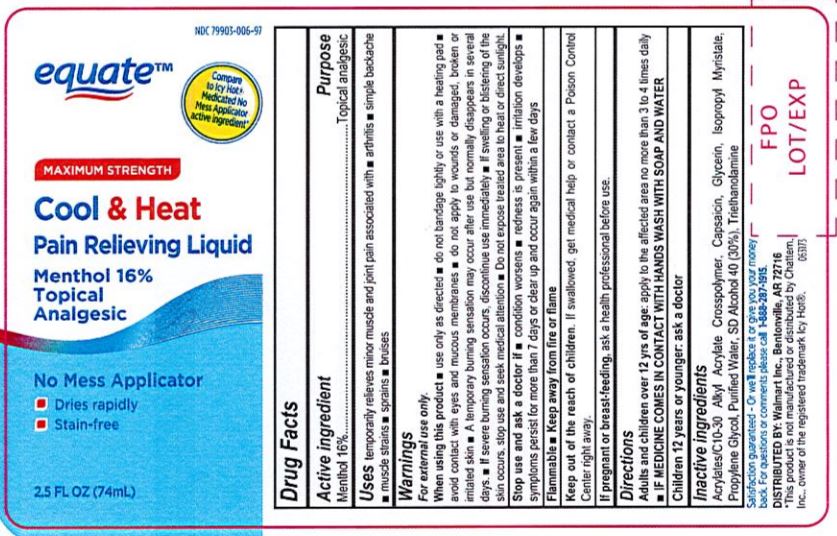 DRUG LABEL: Equate Cool and Heat Pain Relieving Liquid
NDC: 79903-006 | Form: LIQUID
Manufacturer: Walmart, Inc.
Category: otc | Type: HUMAN OTC DRUG LABEL
Date: 20251211

ACTIVE INGREDIENTS: MENTHOL 16 mg/100 mL
INACTIVE INGREDIENTS: GLYCERIN; WATER; (C10-C30)ALKYL METHACRYLATE ESTER; PROPYLENE GLYCOL; TROLAMINE; ALCOHOL; CAPSAICIN; ISOPROPYL MYRISTATE

Equate Cool & Heat Pain Relief

DOSAGE AND ADMINISTRATION

Adults and children over 12 yrs of age: apply to the affected area no more than 3 to 4 times daily

IF MEDICINE COMES IN CONTACT WITH HANDS, WASH WITH SOAP AND WATER.

Children 12 years or younger: ask a doctor.

WARNINGS

Flammable, keep away from fire or flame. When using this product: use only as directed. Do not bandage tightly or use with a heating pad. Avoid contact with eyes and mucous membranes. Do not apply to wounds or damaged, broken or irritated skin. A temporary burning sensation may occur after use but normally disappears in several days. If severe burning sensation occurs, discontinue use immediately. If swelling or blistering of the skin occurs, stop use and seek medical attention. Do not expose treated area to heat or direct sunlight.

INACTIVE INGREDIENT

Acrylates/C10-30 Alkyl Acrylate Crosspolymer, Capsaicin, Glycerin, Isopropyl Myristate, Propylene Glycol, SD Alcohol 40 (30%), Triethanolamine, Purified Water.

INDICATIONS AND USAGE

Temporarily relieves minor muscle and joint pain associated with arthritis, simple backache, muscle strains, sprains, bruises.

Keep out of reach of children. If swallowed, get medical help or contact a Poison Control Center right away.

PURPOSE

Topical analgesic

ACTIVE INGREDIENT

Menthol 16%

PREGNANCY OR BREAST FEEDING

If pregnant or breast feeding, ask a healthcare professional before use.